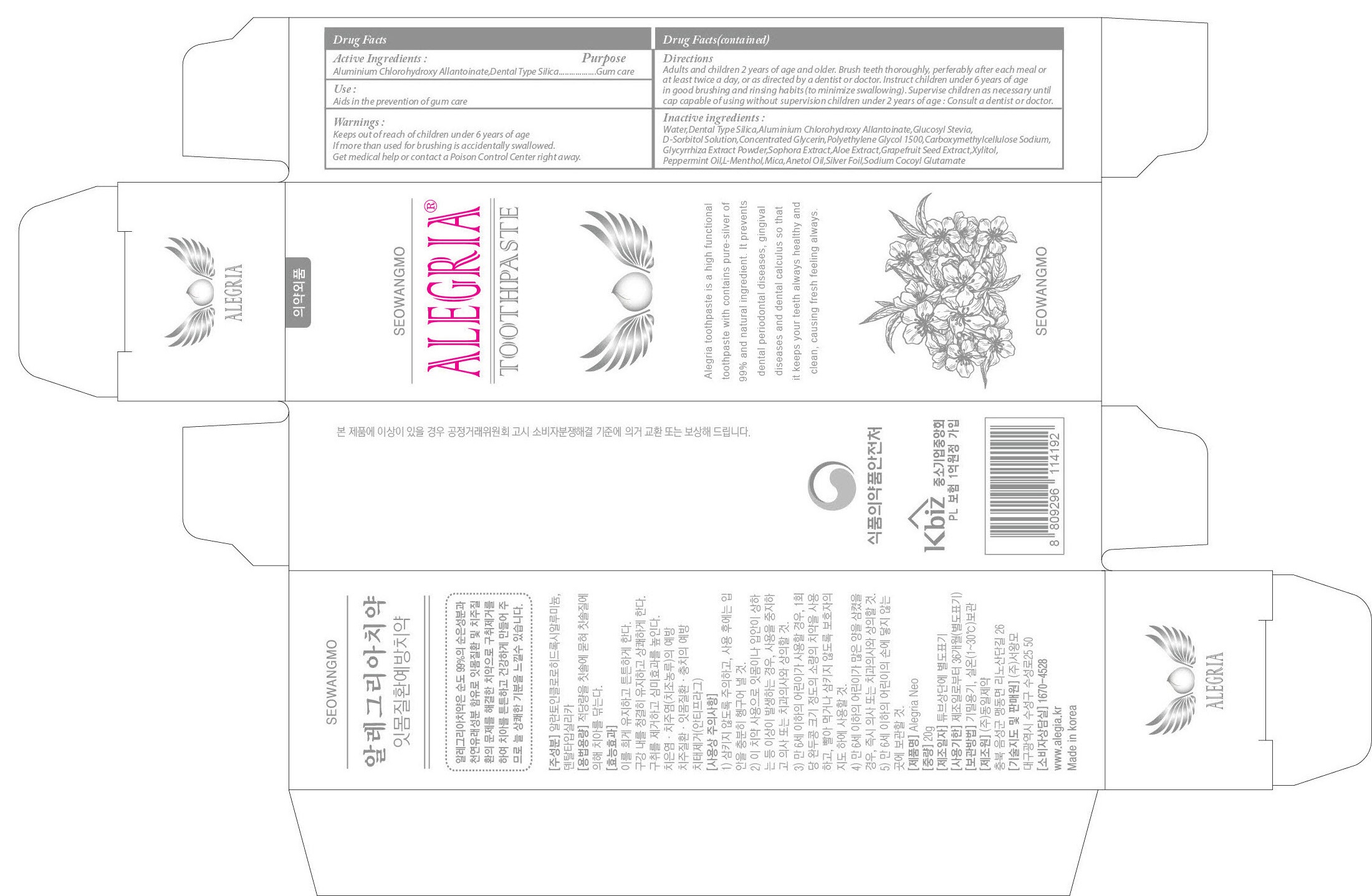 DRUG LABEL: Alegria Neo
NDC: 70406-020 | Form: PASTE, DENTIFRICE
Manufacturer: Seowangmo Corporation
Category: otc | Type: HUMAN OTC DRUG LABEL
Date: 20171103

ACTIVE INGREDIENTS: SILICON DIOXIDE 2.80 g/20 g; Allantoin 0.008 g/20 g
INACTIVE INGREDIENTS: WATER; Xylitol

ACTIVE INGREDIENT

Active Ingredient: Dental Type Silica 14.0%, Aluminium Chlorohydroxy Allantoinate 0.04%

INACTIVE INGREDIENT

Inactive Ingredients: D-Sorbitol Solution, Aqua, Polyethylene Glycol 1500, Mica, Concentrated Glycerin, Sodium Cocoyl Glutamate, Carboxymethylcellulose Sodium, Peppermint Oil, Anetol, Sophora Extract, Grapefruit Seed Extract, Xylitol, Glucosyl Stevia, L-Menthol, Hydroxyapatite, Eucalyptus Extract, Sage Extract, Chamomile Extract, Aloe Extract, Glycyrrhiza Extract Powder, Argentum

PURPOSE

Purpose: Gum Care

WARNINGS

Warnings: If more than used for brushing is accidentally swallowed, get medical help or contact a Poison Control Center right away.

Keep out of reach of children: Keep out of reach of children under 6 years of age.

Use

Use: Aids in the prevention of gum care

Directions

Directions: 1) Adults and children 2 years of age and older: Brush teeth throughly preferably after each meal or at least twice a day or as directed by a dentist or doctor. 2) Children under 6 years: To minimize swallowing, use a pea-sized amount and supervise brushing until good habits are established. 3) Children under 2 years: Consult a dentist or doctor.